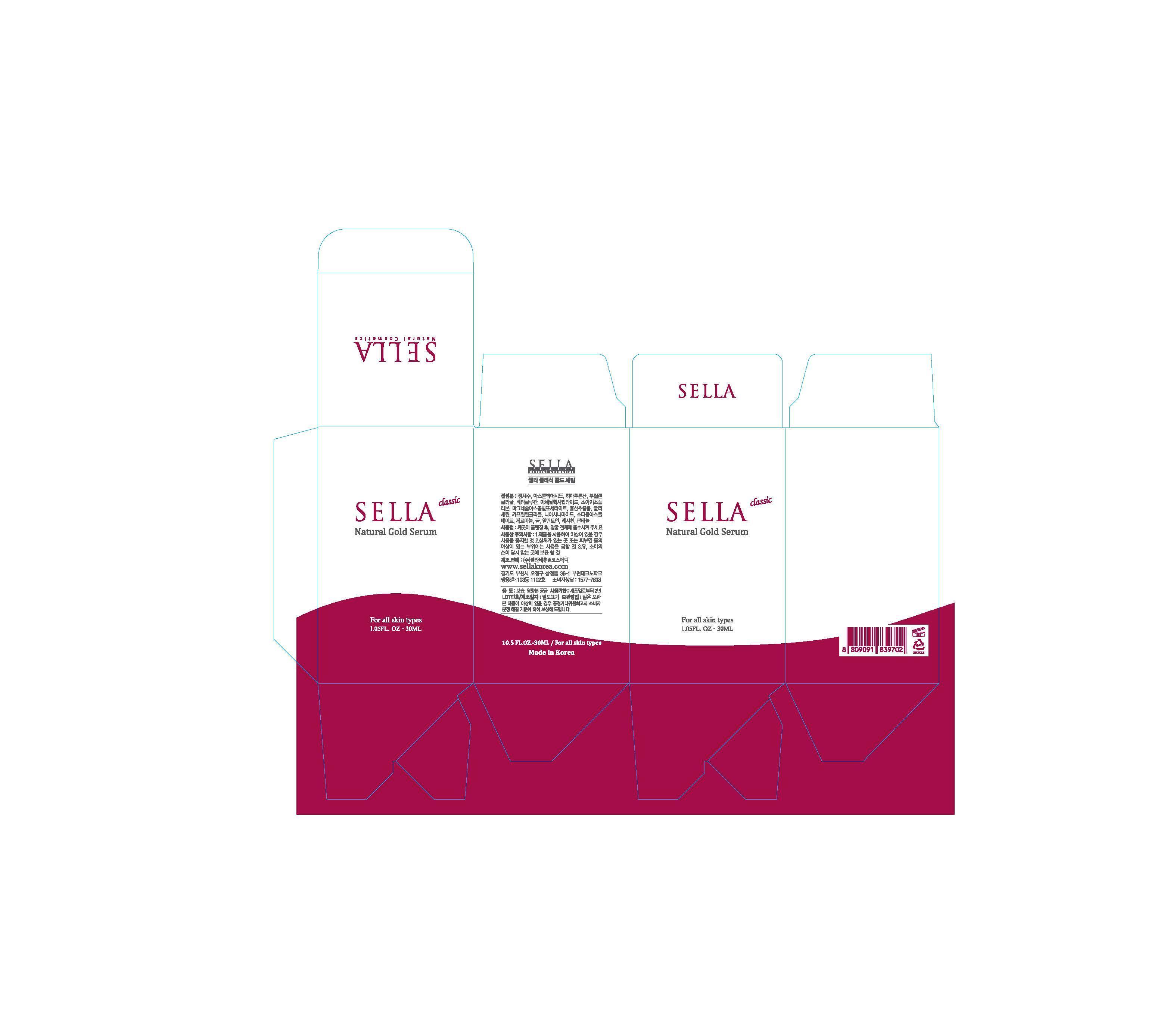 DRUG LABEL: SELLA CLASSIC NATURAL GOLD SERUM
NDC: 69603-0201 | Form: LIQUID
Manufacturer: Sella Natural Cosmetics Co.,Ltd.
Category: otc | Type: HUMAN OTC DRUG LABEL
Date: 20150211

ACTIVE INGREDIENTS: GLYCERIN 4 g/100 mL
INACTIVE INGREDIENTS: WATER; PANTHENOL; ALLANTOIN

Drug Facts

ACTIVE INGREDIENT

glycerine

INACTIVE INGREDIENT

water, butylene glycol, allantoin, panthenol etc

PURPOSE

skin protectant
skin humectant

keep out of reach of the children

INDICATIONS AND USAGE

apply to the skin and rub gently

WARNINGS

・Stop using the product when you have skin problems or the product disagrees with your skin
・Stop using the product immediately and consult a dermatologist if you have redness, swelling, itching or irritation on the skin while or after using the product.
・Don't place the product in any place where it will be subjected to extremely high or low temperatures or direct sunlight.

DOSAGE AND ADMINISTRATION

for external use only